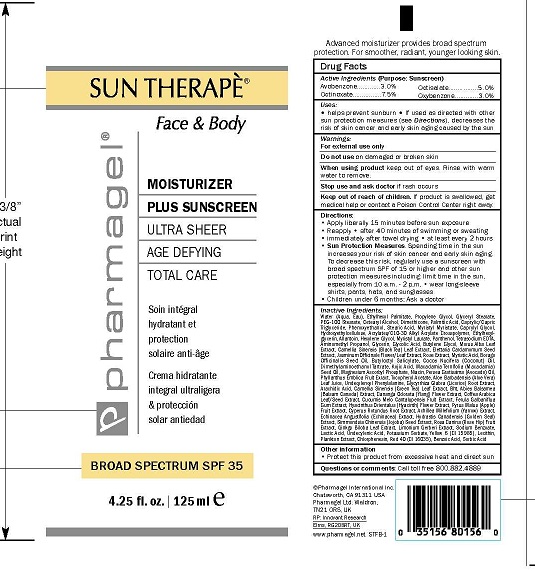 DRUG LABEL: SUN THERAPE FACE AND BODY

NDC: 67879-309 | Form: LOTION
Manufacturer: PHARMAGEL INTERNATIONAL INC
Category: otc | Type: HUMAN OTC DRUG LABEL
Date: 20240813

ACTIVE INGREDIENTS: OCTINOXATE 7.5 g/100 mL; OCTISALATE 5 g/100 mL; OXYBENZONE 3 g/100 mL; AVOBENZONE 3 g/100 mL
INACTIVE INGREDIENTS: WATER; ETHYLHEXYL PALMITATE; PROPYLENE GLYCOL; GLYCERYL MONOSTEARATE; PEG-100 STEARATE; CETOSTEARYL ALCOHOL; DIMETHICONE; PALMITIC ACID; MEDIUM-CHAIN TRIGLYCERIDES; PHENOXYETHANOL; STEARIC ACID; MYRISTYL MYRISTATE; CAPRYLYL GLYCOL; HYDROXYETHYL CELLULOSE (2000 CPS AT 1%); CARBOMER INTERPOLYMER TYPE A (ALLYL SUCROSE CROSSLINKED); ETHYLHEXYLGLYCERIN; ALLANTOIN; HEXYLENE GLYCOL; MYRISTYL LAURATE; PANTHENOL; EDETATE SODIUM; AMINOMETHYLPROPANOL; GLYCERIN; GLYCOLIC ACID; BUTYLENE GLYCOL; MORUS ALBA LEAF; TEA LEAF; CARDAMOM; JASMINUM OFFICINALE FLOWER; ROSA CENTIFOLIA FLOWER; MYRISTIC ACID; BORAGE OIL; BUTYLOCTYL SALICYLATE; COCONUT OIL; DEANOL BITARTRATE; KOJIC ACID; MACADAMIA OIL; MAGNESIUM ASCORBYL PHOSPHATE; NIACIN; AVOCADO OIL; PHYLLANTHUS EMBLICA FRUIT; .ALPHA.-TOCOPHEROL ACETATE; ALOE VERA LEAF; UNDECYLENOYL PHENYLALANINE; GLYCYRRHIZA GLABRA; ARACHIDIC ACID; GREEN TEA LEAF; BUTYLATED HYDROXYTOLUENE; BALSAM FIR LEAFY TWIG; CANANGA ODORATA FLOWER; ARABICA COFFEE BEAN; CANTALOUPE; GALBANUM; HYACINTHUS ORIENTALIS FLOWER; APPLE; CYPERUS ROTUNDUS ROOT; ACHILLEA MILLEFOLIUM; ECHINACEA ANGUSTIFOLIA; GOLDENSEAL; SIMMONDSIA CHINENSIS SEED; ROSA CANINA FRUIT; GINKGO; LIMONIUM GERBERI FLOWERING TOP; SODIUM BENZOATE; LACTIC ACID; UNDECYLENIC ACID; POTASSIUM SORBATE; FD&C YELLOW NO. 6; LECITHIN, SOYBEAN; PHYMATOLITHON CALCAREUM; CHLORPHENESIN; FD&C RED NO. 40; BENZOIC ACID; SORBIC ACID

PHARMAGEL - SUN THERAPE FACE AND BODY (67879-309)

ACTIVE INGREDIENTS

Avobenzone..........................3.0%

Octinoxate............................7.5%

Octisalate.............................5.0%

Oxybenzone..........................3.0%

PURPOSE

SUNSCREEN

USES

• Helps prevent sunburn
• If used as directed with other sun protection measures (see Directions), decreases the risk of skin cancer and early skin aging caused by the sun

WARNINGS

• For external use only
• Do not use on damaged or broken skin
• When using this product keep out of eyes. Rinse with warm water to remove
• Stop use and ask doctor if rash occurs

• Keep out of reach of children. If product is swallowed, get medical help or contact a Poison Control Center right away.

Directions For Sunscreen Use:

• Apply liberally and evenly 15 minutes before sun exposure
• Sun Protection Measures. Spending time in the sun increases your risk of skin cancer and early skin aging. To decrease this risk, regularly use a sunscreen with broad spectrum SPF of 15 or higher and other sun protection measures including:
• Limit time in the sun, especially from 10 a.m.- 2 p.m.
• Wear long-sleeve shirts, pants, hats, and sunglasses
• Reapply at least every 2 hours
• Use a water resistant sunscreen if swimming or sweating
• Children under 6 months: Ask a doctor

INACTIVE INGREDIENTS:

WATER (AQUA), ETHYLHEXYL PALMITATE, PROPYLENE GLYCOL, GLYCERYL STEARATE, PEG-100 STEARATE, CETEARYL ALCOHOL, DIMETHICONE, PALMITIC ACID, CAPRYLIC/CAPRIC TRIGLYCERIDE, PHENOXYETHANOL, STEARIC ACID, MYRISTYL MYRISTATE, CAPRYLYL GLYCOL, HYDROXYETHYLCELLULOSE, ACRYLATES/C10-30 ALKYL ACRYLATE CROSSPOLYMER, ETHYLHEXYLGLYCERIN, ALLANTOIN, HEXYLENE GLYCOL, MYRISTYL LAURATE, PANTHENOL, TETRASODIUM EDTA, AMINOMETHYL PROPANOL, GLYCERIN, GLYCOLIC ACID, BUTYLENE GLYCOL, MORUS ALBA LEAF EXTRACT, CAMELLIA SINENSIS (BLACK TEA) LEAF EXTRACT, ELETTARIA CARDAMOMUM SEED EXTRACT, JASMINUM OFFICINALE FLOWER/LEAF EXTRACT, ROSE EXTRACT, MYRISTIC ACID, BORAGO OFFICINALIS SEED OIL, BUTYLOCTYL SALICYLATE, COCOS NUCIFERA (COCONUT) OIL, DIMETHYLAMINOETHANOL TARTRATE, KOJIC ACID, MACADAMIA TERNIFOLIA (MACADAMIA) SEED OIL, MAGNESIUM ASCORBYL PHOSPHATE, NIACIN, PERSEA GRATISSIMA (AVOCADO) OIL, PHYLLANTHUS EMBLICA FRUIT EXRACT, TOCOPHERYL ACETATE, ALOE BARBADENSIS (ALOE VERA) LEAF JUICE, UNDECYLENOYL PHENYLALANINE, GLYCYRRHIZA GLABRA (LICORICE) ROOT EXTRACT, ARACHIDIC ACID, CAMELLIA SINENSIS (GREEN TEA) LEAF EXTRACT, BHT, ABIES BALSAMEA (BALSAM CANADA) EXTRACT, CANANGA ODORATA (YLANG) FLOWER EXTRACT, COFFEA ARABICA LEAF/SEED EXTRACT, CUCUMIS MELO CANTALUPENSIS FRUIT EXTRACT, FERULA GALBANIFLUA GUM EXTRACT, HYACINTHUS ORIENTALUS (HYACINTHUS) FLOWER EXTRACT, PYRUS MALUS (APPLE) FRUIT EXTRACT, CYPERUS ROTUNDUS ROOT EXTRACT, ACHILLEA MILLEFOLIUM (YARROW) EXTRACT, ECHINACEA ANGUSTIFOLIA (ECHINACEA) EXTRACT, HYDRASTIS CANADENSIS (GOLDEN SEAL) EXTRACT, SIMMONDSIA CHINENSIS (JOJOBA) SEED EXTRACT, ROSA CANINA (ROSE HIP) FRUIT EXTRACT, GINKGO BILOBA LEAF EXTRACT, LIMONIUM GERBERI EXTRACT, SODIUM BENZOATE, LACTIC ACID, UNDECYLENIC ACID, POTASSIUM SORBATE, YELLOW 6 (CI 15985), LECITHIN, PLANKTON EXTRACT, CHLORPHENESIN, RED 40 (CI 16035), BENZOIC ACID, SORBIC ACID

OTHER INFORMATION

- PROTECT THIS PRODUCT FROM EXCESSIVE HEAT AND DIRECT SUN

Questions or Comments?

Call toll free 800-882-4889